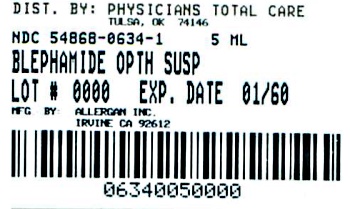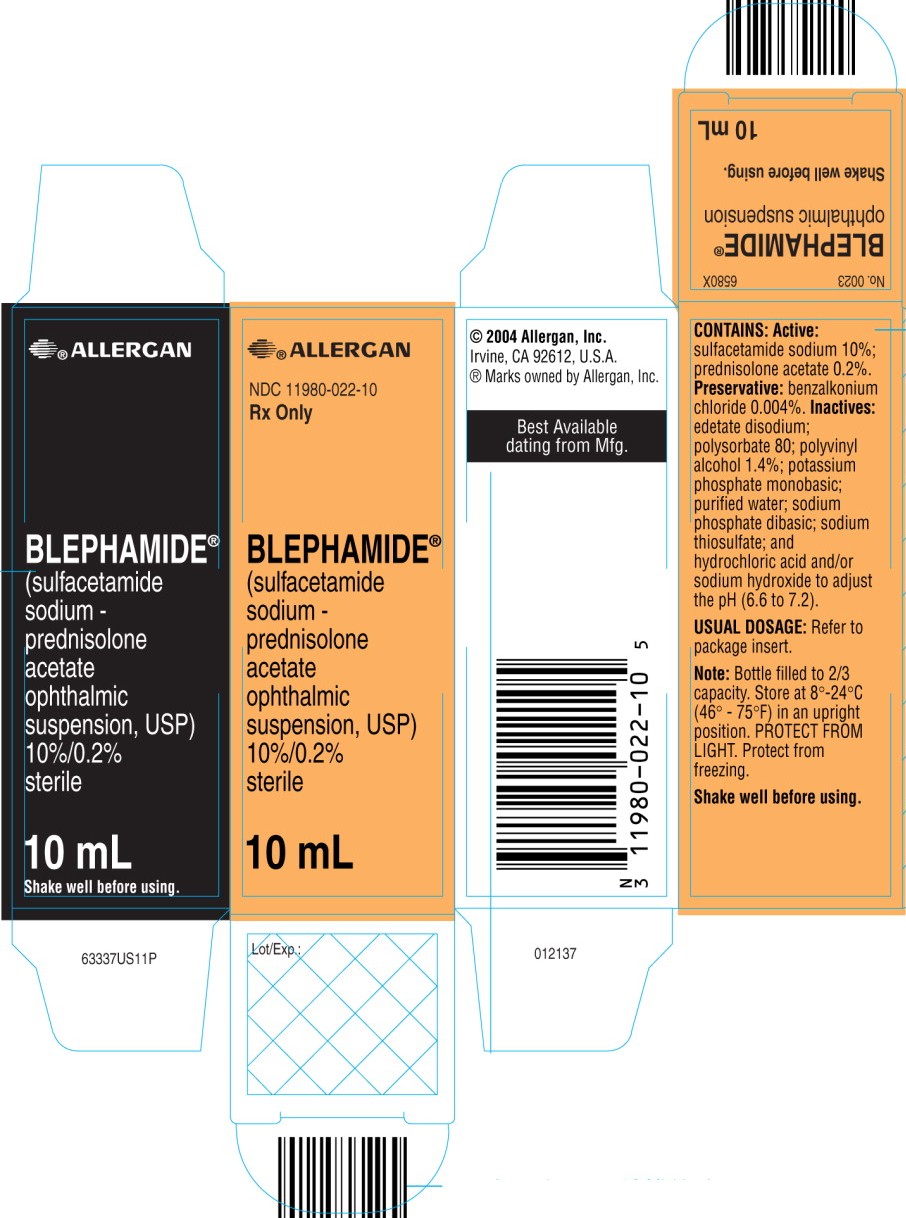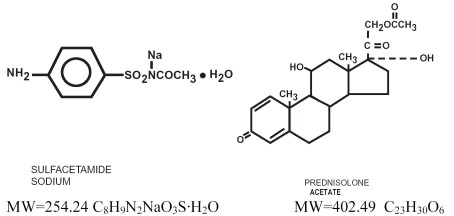 DRUG LABEL: BLEPHAMIDE
NDC: 54868-0634 | Form: SUSPENSION/ DROPS
Manufacturer: Physicians Total Care, Inc.
Category: prescription | Type: HUMAN PRESCRIPTION DRUG LABEL
Date: 20131115

ACTIVE INGREDIENTS: sulfacetamide sodium 100 mg/1 mL; prednisolone acetate 2 mg/1 mL
INACTIVE INGREDIENTS: benzalkonium chloride; edetate disodium; polysorbate 80; polyvinyl alcohol; potassium phosphate, monobasic; water; sodium phosphate, dibasic; sodium thiosulfate; hydrochloric acid; sodium hydroxide

BLEPHAMIDE®
(sulfacetamide sodium – prednisolone acetate ophthalmic suspension, USP) 10%/0.2%

DESCRIPTION

BLEPHAMIDE® ophthalmic suspension is a topical anti-inflammatory/anti-infective combination product for ophthalmic use.

Structural Formulas:

Chemical Names:

Sulfacetamide sodium: N-sulfanilylacetamide monosodium salt monohydrate.

Prednisolone acetate: 11ß, 17, 21-trihydroxypregna-1, 4-diene-3, 20-dione 21-acetate.

Contains:

Actives: sulfacetamide sodium 10%, prednisolone acetate (microfine suspension) 0.2%.

Preservative: benzalkonium chloride (0.004%). Inactives: edetate disodium; polysorbate 80; polyvinyl alcohol 1.4%; potassium phosphate, monobasic; purified water; sodium phosphate, dibasic; sodium thiosulfate; hydrochloric acid and/or sodium hydroxide to adjust the pH (6.6 to 7.2).

CLINICAL PHARMACOLOGY

Corticosteroids suppress the inflammatory response to a variety of agents and they probably delay or slow healing. Since corticosteroids may inhibit the body's defense mechanism against infection, a concomitant antibacterial drug may be used when this inhibition is considered to be clinically significant in a particular case.

When a decision to administer both a corticosteroid and an antibacterial is made, the administration of such drugs in combination has the advantage of greater patient compliance and convenience, with the added assurance that the appropriate dosage of both drugs is administered. When both types of drugs are in the same formulation, compatibility of ingredients is assured and the correct volume of drug is delivered and retained. The relative potency of corticosteroids depends on the molecular structure, concentration and release from the vehicle.

MICROBIOLOGY

Microbiology: Sulfacetamide sodium exerts a bacteriostatic effect against susceptible bacteria by restricting the synthesis of folic acid required for growth through competition with p-aminobenzoic acid.

Some strains of these bacteria may be resistant to sulfacetamide or resistant strains may emerge in vivo.

The anti-infective component in these products is included to provide action against specific organisms susceptible to it. Sulfacetamide sodium is active in vitro against susceptible strains of the following microorganisms: Escherichia coli, Staphylococcus aureus, Streptococcus pneumoniae, Streptococcus (viridans group), Haemophilus influenzae, Klebsiella species, and Enterobacter species. This product does not provide adequate coverage against: Neisseria species, Pseudomonas species, and Serratia marcescens (see INDICATIONS AND USAGE).

INDICATIONS AND USAGE

A steroid/anti-infective combination is indicated for steroid-responsive inflammatory ocular conditions for which a corticosteroid is indicated and where superficial bacterial ocular infection or a risk of bacterial ocular infection exists.

Ocular corticosteroids are indicated in inflammatory conditions of the palpebral and bulbar conjunctiva, cornea, and anterior segment of the globe where the inherent risk of corticosteroid use in certain infective conjunctivitides is accepted to obtain diminution in edema and inflammation. They are also indicated in chronic anterior uveitis and corneal injury from chemical, radiation or thermal burns or penetration of foreign bodies.

The use of a combination drug with an anti-infective component is indicated where the risk of superficial ocular infection is high or where there is an expectation that potentially dangerous numbers of bacteria will be present in the eye.

The particular antibacterial drug in this product is active against the following common bacterial eye pathogens: Escherichia coli, Staphylococcus aureus, Streptococcus pneumoniae, Streptococcus (viridans group), Haemophilus influenzae, Klebsiella species, and Enterobacter species. This product does not provide adequate coverage against: Neisseria species, Pseudomonas species, and Serratia marcescens.

A significant percentage of staphylococcal isolates are completely resistant to sulfa drugs.

CONTRAINDICATIONS

BLEPHAMIDE® ophthalmic suspension is contraindicated in most viral diseases of the cornea and conjunctiva including epithelial herpes simplex keratitis (dendritic keratitis), vaccinia, and varicella, and also in mycobacterial infection of the eye and fungal diseases of ocular structures.

This product is also contraindicated in individuals with known or suspected hypersensitivity to any of the ingredients of this preparation, to other sulfonamides and to other corticosteroids. See WARNINGS. (Hypersensitivity to the antimicrobial component occurs at a higher rate than for other components.)

WARNINGS

NOT FOR INJECTION INTO THE EYE.

Prolonged use of corticosteroids may result in ocular hypertension/glaucoma with damage to the optic nerve, defects in visual acuity and fields of vision, and in posterior subcapsular cataract formation.

Acute anterior uveitis may occur in susceptible individuals, primarily Blacks.

Prolonged use of BLEPHAMIDE® ophthalmic suspension may suppress the host response and thus increase the hazard of secondary ocular infections. In those diseases causing thinning of the cornea or sclera, perforation has been known to occur with the use of topical corticosteroids. In acute purulent conditions of the eye, corticosteroids may mask infection or enhance existing infection.

If the product is used for 10 days or longer, intraocular pressure should be routinely monitored even though it may be difficult in children and uncooperative patients. Corticosteroids should be used with caution in the presence of glaucoma. Intraocular pressure should be checked frequently.

A significant percentage of staphylococcal isolates are completely resistant to sulfonamides.

The use of steroids after cataract surgery may delay healing and increase the incidence of filtering blebs.

The use of ocular corticosteroids may prolong the course and may exacerbate the severity of many viral infections of the eye (including herpes simplex). Employment of corticosteroid medication in the treatment of herpes simplex requires great caution.

Topical steroids are not effective in mustard gas keratitis and Sjögren's keratoconjunctivitis.

Fatalities have occurred, although rarely, due to severe reactions to sulfonamides including Stevens-Johnson syndrome, toxic epidermal necrolysis, fulminant hepatic necrosis, agranulocytosis, aplastic anemia and other blood dyscrasias. Sensitization may recur when a sulfonamide is readministered, irrespective of the route of administration.

If signs of hypersensitivity or other serious reactions occur, discontinue use of this preparation. Cross-sensitivity among corticosteroids has been demonstrated (see ADVERSE REACTIONS).

PRECAUTIONS

General:

The initial prescription and renewal of the medication order beyond 20 milliliters of the suspension should be made by a physician only after examination of the patient with the aid of magnification, such as slit lamp biomicroscopy and, where appropriate, fluorescein staining. If signs and symptoms fail to improve after two days, the patient should be re-evaluated.

The possibility of fungal infections of the cornea should be considered after prolonged corticosteroid dosing. Use with caution in patients with severe dry eye. Fungal cultures should be taken when appropriate.

The p-aminobenzoic acid present in purulent exudates competes with sulfonamides and can reduce their effectiveness.

Information for Patients:

If inflammation or pain persists longer than 48 hours or becomes aggravated, the patient should be advised to discontinue use of the medication and consult a physician (see WARNINGS).

Contact lenses should not be worn during the use of this product.

This product is sterile when packaged. To prevent contamination, care should be taken to avoid touching the applicator tip to eyelids or to any other surface. The use of this bottle by more than one person may spread infection. Keep bottle tightly closed when not in use. Protect from light. Sulfonamide solutions darken on prolonged standing and exposure to heat and light. Do not use if solution has darkened. Yellowing does not affect activity. Keep out of the reach of children.

Laboratory Tests:

Eyelid cultures and tests to determine the susceptibility of organisms to sulfacetamide may be indicated if signs and symptoms persist or recur in spite of the recommended course of treatment with BLEPHAMIDE® ophthalmic suspension.

Drug Interactions:

BLEPHAMIDE® ophthalmic suspension is incompatible with silver preparations. Local anesthetics related to p-aminobenzoic acid may antagonize the action of the sulfonamides.

Carcinogenesis, Mutagenesis, Impairment of Fertility:

Prednisolone has been reported to be noncarcinogenic. Long-term animal studies for carcinogenic potential have not been performed with sulfacetamide.

One author detected chromosomal nondisjunction in the yeast Saccharomyces cerevisiae following application of sulfacetamide sodium. The significance of this finding to topical ophthalmic use of sulfacetamide sodium in the human is unknown.

Mutagenic studies with prednisolone have been negative. Studies on reproduction and fertility have not been performed with sulfacetamide. A long-term chronic toxicity study in dogs showed that high oral doses of prednisolone prevented estrus. A decrease in fertility was seen in male and female rats that were mated following oral dosing with another glucocorticosteroid.

Pregnancy:

Teratogenic Effects: Pregnancy Category C. Animal reproduction studies have not been conducted with sulfacetamide sodium. Prednisolone has been shown to be teratogenic in rabbits, hamsters, and mice. In mice, prednisolone has been shown to be teratogenic when given in doses 1 to 10 times the human ocular dose. Dexamethasone, hydrocortisone and prednisolone were ocularly applied to both eyes of pregnant mice five times per day on days 10 through 13 of gestation. A significant increase in the incidence of cleft palate was observed in the fetuses of the treated mice. There are no adequate well-controlled studies in pregnant women dosed with corticosteroids.

Kernicterus may be precipitated in infants by sulfonamides being given systemically during the third trimester of pregnancy. It is not known whether sulfacetamide sodium can cause fetal harm when administered to a pregnant woman or whether it can affect reproductive capacity.

BLEPHAMIDE® ophthalmic suspension should be used during pregnancy only if the potential benefit justifies the potential risk to the fetus.

Nursing Mothers:

It is not known whether topical administration of corticosteroids could result in sufficient systemic absorption to produce detectable quantities in human milk. Systemically administered corticosteroids appear in human milk and could suppress growth, interfere with endogenous corticosteroid production, or cause other untoward effects. Systemically administered sulfonamides are capable of producing kernicterus in infants of lactating women. Because of the potential for serious adverse reactions in nursing infants from sulfacetamide sodium and prednisolone acetate ophthalmic suspensions, a decision should be made whether to discontinue nursing or to discontinue the medication.

Pediatric Use:

Safety and effectiveness in pediatric patients below the age of six have not been established.

ADVERSE REACTIONS

Adverse reactions have occurred with corticosteroid/antibacterial combination drugs which can be attributed to the corticosteroid component, the antibacterial component, or the combination. Exact incidence figures are not available since no denominator of treated patients is available.

Reactions occurring most often from the presence of the antibacterial ingredient are allergic sensitizations. Fatalities have occurred, although rarely, due to severe reactions to sulfonamides including Stevens-Johnson syndrome, toxic epidermal necrolysis, fulminant hepatic necrosis, agranulocytosis, aplastic anemia, and other blood dyscrasias (See WARNINGS).

Sulfacetamide sodium may cause local irritation.

The reactions due to the corticosteroid component in decreasing order of frequency are: elevation of intraocular pressure (IOP) with possible development of glaucoma and infrequent optic nerve damage, posterior subcapsular cataract formation, and delayed wound healing.

Although systemic effects are extremely uncommon, there have been rare occurrences of systemic hypercorticoidism after use of topical corticosteroids.

Corticosteroid-containing preparations can also cause acute anterior uveitis or perforation of the globe. Mydriasis, loss of accommodation and ptosis have occasionally been reported following local use of corticosteroids.

Secondary infection: The development of secondary infection has occurred after use of combinations containing corticosteroids and antibacterials. Fungal and viral infections of the cornea are particularly prone to develop coincidentally with long-term applications of corticosteroid. The possibility of fungal invasion must be considered in any persistent corneal ulceration where corticosteroid treatment has been used.

Secondary bacterial ocular infection following suppression of host responses also occurs.

DOSAGE AND ADMINISTRATION

SHAKE WELL BEFORE USING. Two drops should be instilled into the conjunctival sac every four hours during the day and at bedtime.

Not more than 20 milliliters should be prescribed initially, and the prescription should not be refilled without further evaluation as outlined in PRECAUTIONS above.

BLEPHAMIDE® dosage may be reduced, but care should be taken not to discontinue therapy prematurely. In chronic conditions, withdrawal of treatment should be carried out by gradually decreasing the frequency of application.

If signs and symptoms fail to improve after two days, the patient should be re-evaluated (see PRECAUTIONS).

HOW SUPPLIED

BLEPHAMIDE® (sulfacetamide sodium–prednisolone acetate ophthalmic suspension, USP) is supplied sterile in opaque white LDPE plastic bottles and white dropper tips with white high impact polystyrene (HIPS) caps as follows:

5 mL in 10 mL bottle — NDC 54868-0634-1
10 mL in 15 mL bottle

Note: Protect from freezing. Shake well before using.

STORAGE AND HANDLING

Storage: Store at 8°-24°C (46°-75°F) in an upright position.

PROTECT FROM LIGHT.

Sulfonamide solutions darken on prolonged standing and exposure to heat and light. Do not use if solution has darkened. Yellowing does not affect activity.

KEEP OUT OF REACH OF CHILDREN.

Rx only

Revised June 2004

© 2004 Allergan, Inc.
Irvine, CA 92612, U.S.A.
® marks owned by Allergan, Inc.
6580X
71735US10P

Distributed by:
Physicians Total Care, Inc.
Tulsa, OK 74146

Carton PDP

ALLERGAN

Rx Only

BLEPHAMIDE®

(sulfacetamide

sodium -

prednisolone

acetate

ophthalmic

suspension, USP)

10%/0.2%

sterile

10 mL